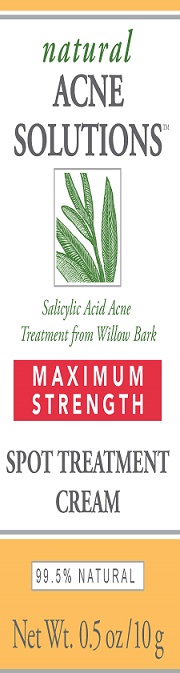 DRUG LABEL: NAS MAX STRENGTH SPOT TREATMENT
NDC: 26052-022 | Form: CREAM
Manufacturer: BURT'S BEES, INC.
Category: otc | Type: HUMAN OTC DRUG LABEL
Date: 20181203

ACTIVE INGREDIENTS: SALICYLIC ACID 2 g/100 g
INACTIVE INGREDIENTS: CYMBOPOGON SCHOENANTHUS TOP; SIMMONDSIA CHINENSIS SEED; GLYCERYL STEARATE SE; PHENOXYETHANOL; TOCOPHEROL; SOYBEAN OIL; STEARYL ALCOHOL; SALIX NIGRA BARK; WATER; GLYCERIN; CETYL ALCOHOL; WHITE WAX; TAMANU OIL; GLYCYRRHIZINATE DIPOTASSIUM; HAMAMELIS VIRGINIANA LEAF; STEARIC ACID; HUMULUS LUPULUS WHOLE; HYDRASTIS CANADENSIS WHOLE; LONICERA CAPRIFOLIUM FLOWER; LECITHIN, SOYBEAN; GLUCOSE OXIDASE; LACTOPEROXIDASE BOVINE; XANTHAN GUM; MEDIUM-CHAIN TRIGLYCERIDES; LONICERA JAPONICA FLOWER; POTASSIUM STEARATE

NATURAL ACNE SOLUTIONS MAXIMUM STRENGTH SPOT TREATMENT CREAM

ACTIVE INGREDIENT

SALICYLIC ACID 2.0%

PURPOSE

ACNE TREATMENT

USES

PENETRATES PORES TO CONTROL ACNE.

WARNINGS

FOR EXTERNAL USE ONLY. USING OTHER TOPICAL ACNE MEDICATION AT THE SAME TIME OR IMMEDIATELY FOLLOWING USE OF THIS PRODUCT MAY INCREASE DRYNESS OR IRRITATION OF THE SKIN. IF THIS OCCURS, ONLY ONE MEDICATION SHOULD BE USED UNLESS DIRECTED BY A DOCTOR.

KEEP OUT OF REACH OF CHILDREN

IF SWALLOWED, GET MEDICAL HELP OR CALL A POISON CONTROL CENTER RIGHT AWAY.

DIRECTIONS

CLEANSE THE SKIN THOROUGHLY BEFORE APPLYING MEDICATION. ON ANY AND ALL ACTIVE BLEMISHES, START WITH ONE APPLICATION DAILY THEN GRADUALLY INCREASE TO 2 OR 3 APPLICATIONS DAILY IF NEEDED. IF BOTHERSOME DRYNESS OR PEELING OCCURS, REDUCE APPLICATION TO ONCE A DAY OR EVERY OTHER DAY.

INACTIVE INGREDIENTS

WATER, CAPRYLIC/CAPRIC TRIGLYCERIDE, GLYCERIN, SALIX NIGRA (WILLOW) BARK EXTRACT, STEARYL ALCOHOL, CETYL ALCOHOL, GLYCERYL STEARATE, BEESWAX, CALOPHYLLUM INOPHYLLUM SEED OIL, CYMBOPOGON SCHOENANTHUS EXTRACT, DIPOTASSIUM GLYCYRRHIZATE, EQUSETUM HIEMALE EXTRACT, HAMAMELIS VIRGINIANA (WITCH HAZEL) LEAF EXTRACT, HUMULUS LUPULUS (HOPS) EXTRACT, HYDRASTIS CANADENSIS (GOLDENSEAL) EXTRACT, LONICERA CAPRIFULIUM EXTRACT, LONICERA JAPONICA EXTRACT, SIMMONDSIA CHINENSIS (JOJOBA) SEED OIL, STEARIC ACID, SORBIC ACID, TOCOPHEROL, XANTHAN GUM, LECITHIN, GLUCOSE, GLYCINE SOJA (SOYBEAN) OIL, FRAGRANCE, SODIUM CHLORIDE, GLUCOSE OXIDASE, LACTOPEROXIDASE, PHENOXYETHANOL.

QUESTIONS?

800-849-7112 OR WWW.BURTSBEES.COM

PDP

BURT'S BEES

NATURAL ACNE SOLUTIONS

MAXIMUM STRENGTH

SPOT TREATMENT CREAM

NET WT. 0.5 OZ.

10 G